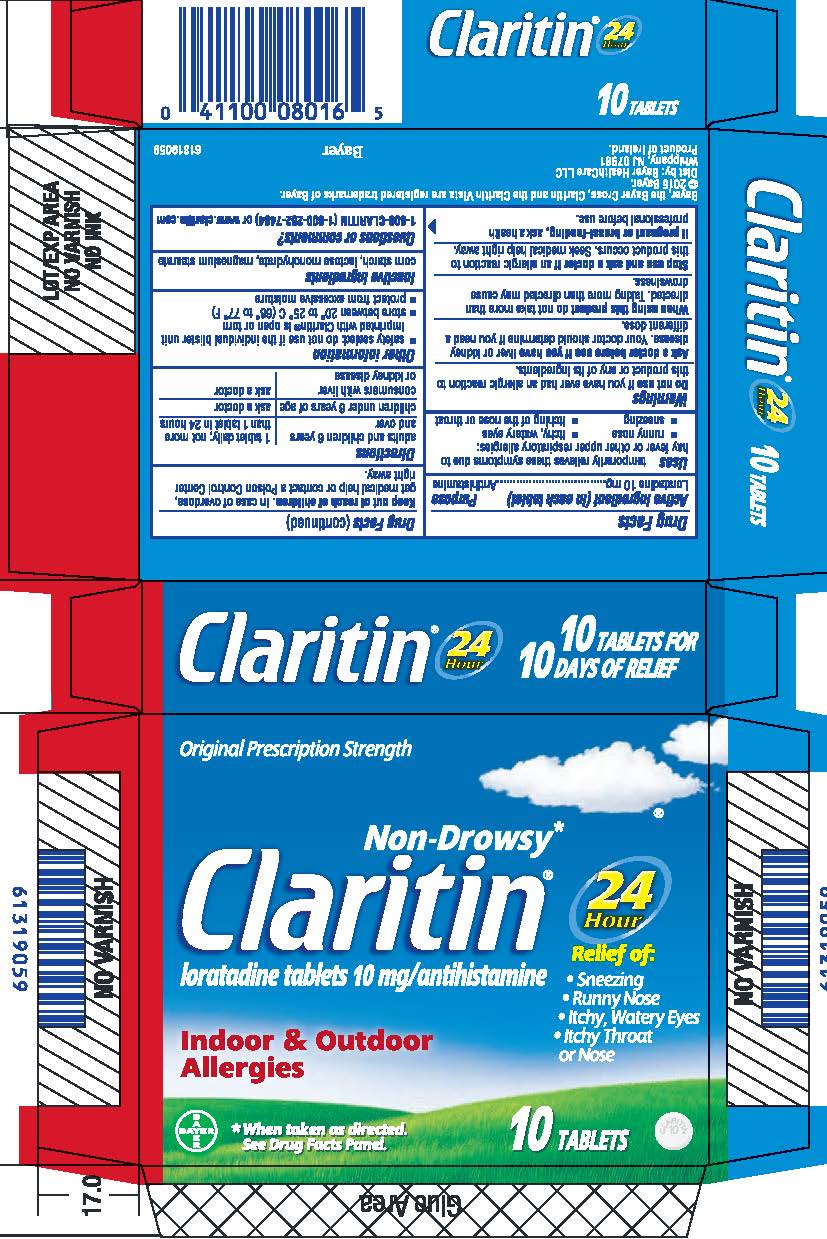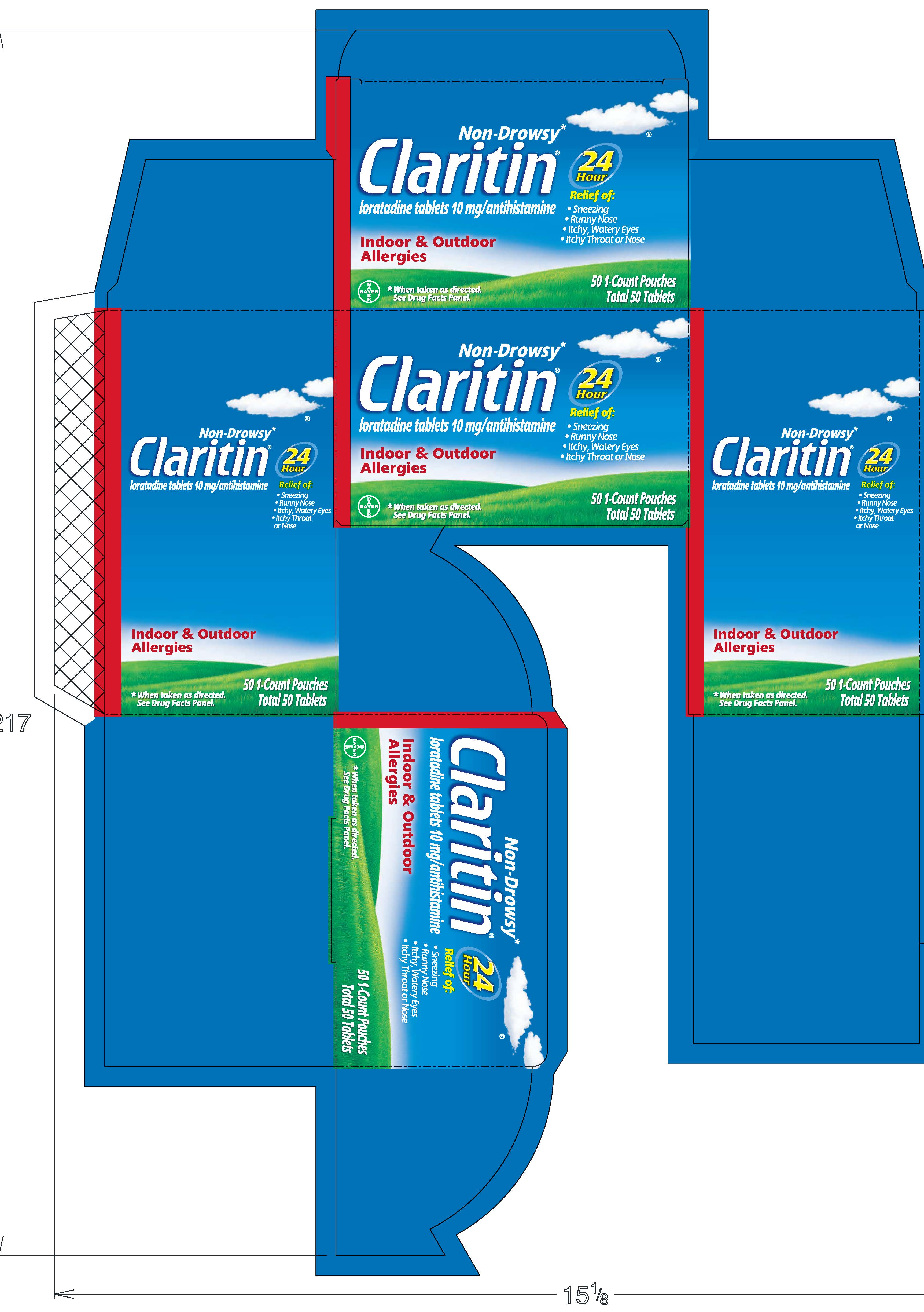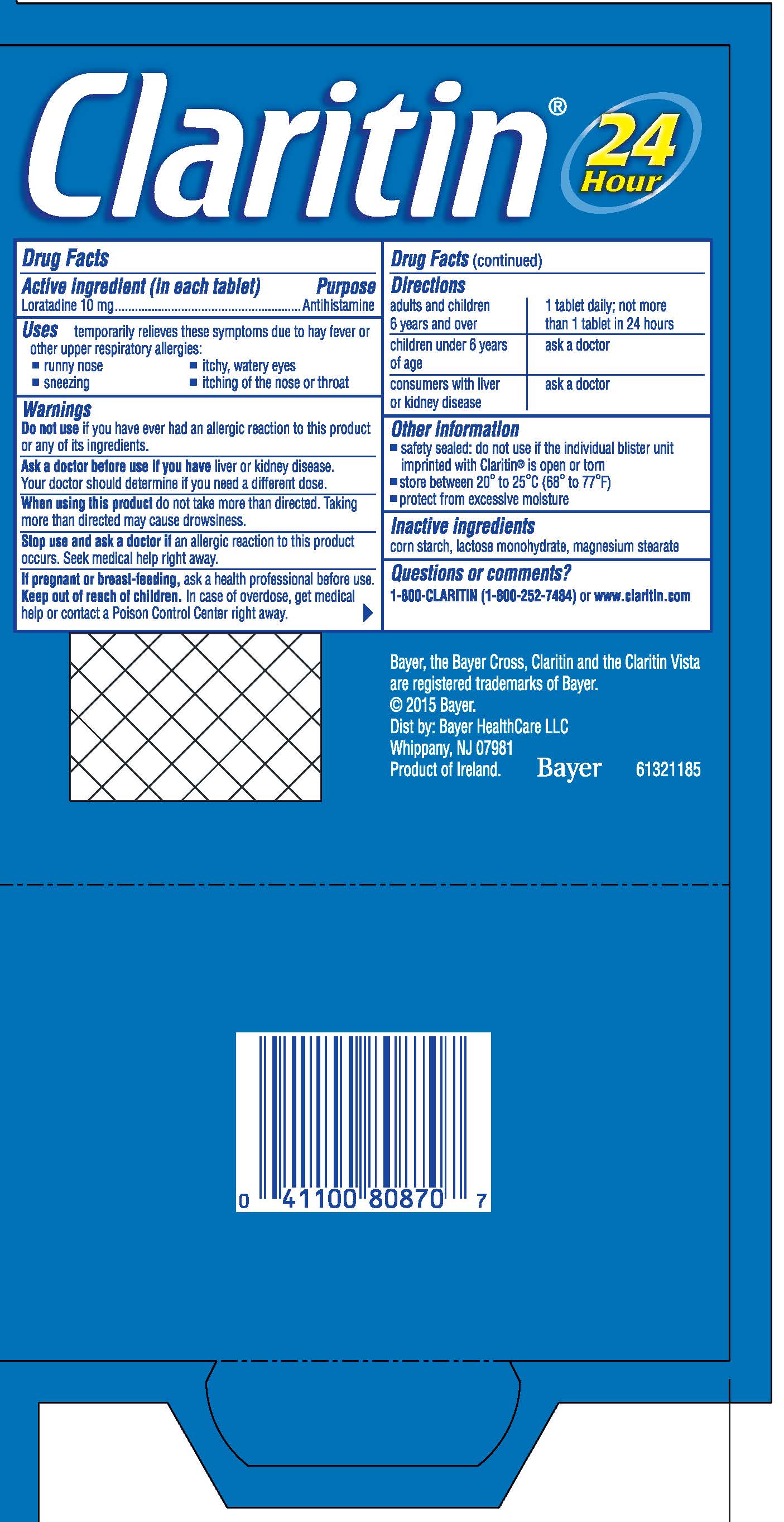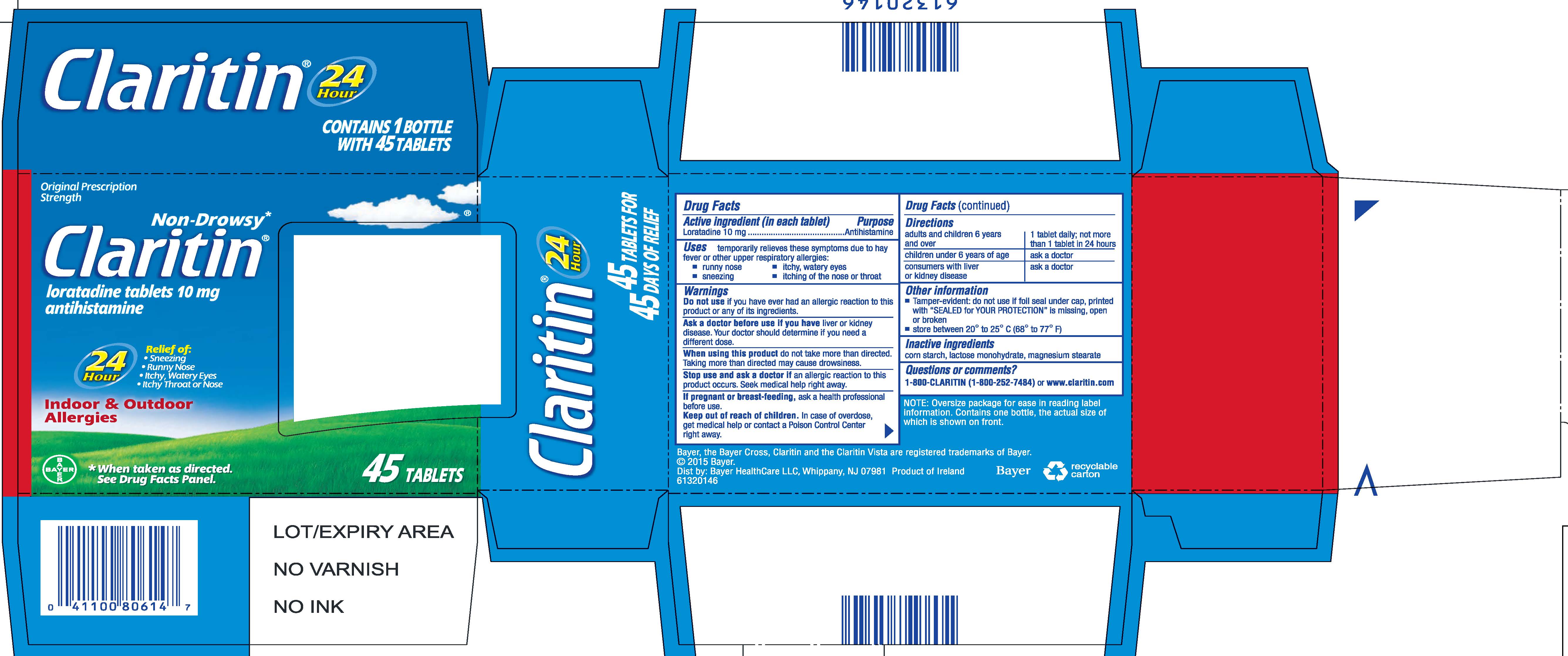 DRUG LABEL: Claritin
NDC: 11523-7237 | Form: TABLET
Manufacturer: Bayer HealthCare LLC.
Category: otc | Type: HUMAN OTC DRUG LABEL
Date: 20251205

ACTIVE INGREDIENTS: LORATADINE 10 mg/1 1
INACTIVE INGREDIENTS: STARCH, CORN; LACTOSE MONOHYDRATE; MAGNESIUM STEARATE

Non-Drowsy*Claritin®
loratadine tablets 10 mg/antihistamine

Drug Facts

Active ingredient (in each tablet)

Loratadine 10 mg

Purpose

Antihistamine

Uses

temporarily relieves these symptoms due to hay fever or other upper respiratory allergies:

- runny nose
- itchy, watery eyes
- sneezing
- itching of the nose or throat

Warnings

Do not use if you have ever had an allergic reaction to this product or any of its ingredients.

Ask a doctor before use if you have liver or kidney disease. Your doctor should determine if you need a different dose.

When using this product do not take more than directed. Taking more than directed may cause drowsiness.

Stop use and ask a doctor if an allergic reaction to this product occurs. Seek medical help right away.

PREGNANCY OR BREAST FEEDING

If pregnant or breast-feeding, ask a health professional before use.

Keep out of reach of children. In case of overdose, get medical help or contact a Poison Control Center right away.

Directions

adults and children 6 years and over | 1 tablet daily; not more than 1 tablet in 24 hours
children under 6 years of age | ask a doctor
consumers with liver or kidney disease | ask a doctor

Other information (Blister foil units)

- safety sealed: do not use if the individual blister unit imprinted with Claritin® is open or torn
- store between 20° to 25°C (68° to 77°F)
- protect from excessive moisture

Other information (Bottles)

- Tamper-evident: do not use if foil seal under cap, printed with "SEALED for YOUR PROTECTION" is missing, open or broken
- store between 20° to 25°C (68° to 77°F)

Inactive ingredients

corn starch, lactose monohydrate, magnesium stearate

Questions or comments?

1-800-CLARITIN (1-800-252-7484) or www.claritin.com

PRINCIPAL DISPLAY PANEL - 10 Tablet Carton

Original Prescription
Strength

Non-Drowsy*
Claritin®
loratadine tablets 10 mg/antihistamine

24 Hour

Relief of:

- Sneezing
- Runny Nose
- Itchy, Watery Eyes
- Itchy Throat or Nose

Indoor & Outdoor

Allergies

*When taken as directed.
See Drug Facts Panel.

10 Tablets

PRINCIPAL DISPLAY PANEL - 45 Count Window Box

Original Prescription Strength

Non-Drowsy *
Claritin ®
loratadine tablets 10 mg/antihistamine

24 Hour

Relief of:

Sneezing
Runny Nose
Itchy, Watery Eyes
Itchy Throat or Nose

Indoor & Outdoor
Allergies

* When taken as directed.
See Drug Facts Panel.

45 TABLETS

PRINCIPAL DISPLAY PANEL - 50 Tablet Carton

Non-Drowsy*
Claritin®
loratadine tablets 10 mg/antihistamine

24 Hour

Relief of:

- Sneezing
- Runny Nose
- Itchy, Watery Eyes
- Itchy Throat or Nose

Indoor & Outdoor
Allergies

*When taken as directed.
See Drug Facts Panel.

50 1-Count Pouches
Total 50 Tablets